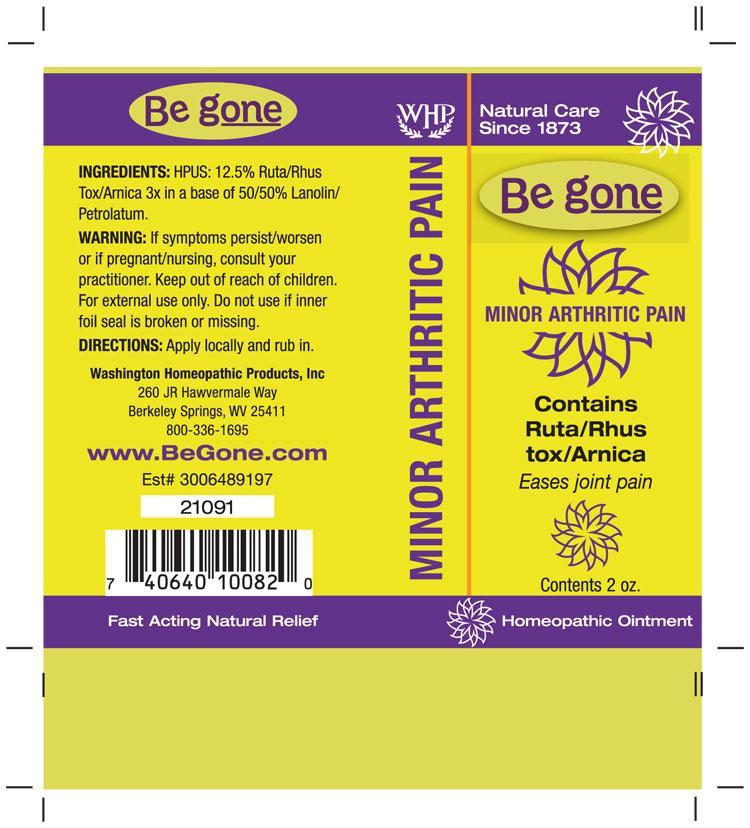 DRUG LABEL: Be gone Minor Arthritic Pain
NDC: 68428-720 | Form: OINTMENT
Manufacturer: Washington Homeopathic Products
Category: homeopathic | Type: HUMAN OTC DRUG LABEL
Date: 20191223

ACTIVE INGREDIENTS: ARNICA MONTANA 3 [hp_X]/56 g; TOXICODENDRON PUBESCENS LEAF 3 [hp_X]/56 g; RUTA GRAVEOLENS FLOWERING TOP 3 [hp_X]/56 g
INACTIVE INGREDIENTS: PETROLATUM; LANOLIN

DRUG FACTS

ACTIVE INGREDIENTS

ARNICA MONTANA 3X

RHUS TOXICODENDRON 3X

RUTA GRAVEOLENS 3X

USES

To relieve joint pain.

KEEP OUT OF REACH OF CHILDREN

Keep this and all medicines out of reach of children.

INDICATIONS

ARNICA MONTANA Bruises

RHUS TOXICODENDRON Better motion

RUTA GRAVEOLENS Bruised feeling

STOP USE AND ASK DOCTOR

For external use only. If symptoms persist/worsen or if pregnant/nursing, consult your practitioner.

DIRECTIONS

Apply locally and rub in.

INACTIVE INGREDIENTS

50% Lanolin

50% Petrolatum

PRINCIPAL DISPLAY PANEL

WHP Be g oneTM Minor Arthritic Pain tube